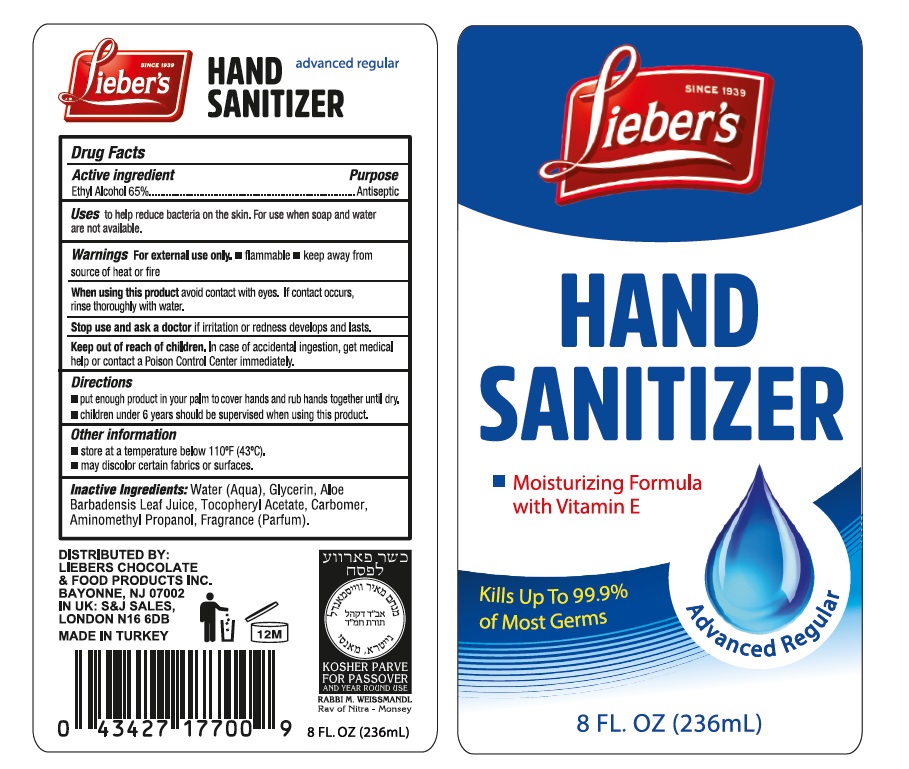 DRUG LABEL: Liebers Hand Sanitizer
NDC: 76772-018 | Form: GEL
Manufacturer: TSM ITHALAT IHRACAT SANAYI VE DIS TICARET LIMITED SIRKETI
Category: otc | Type: HUMAN OTC DRUG LABEL
Date: 20200925

ACTIVE INGREDIENTS: ALCOHOL 0.65 mL/1 mL
INACTIVE INGREDIENTS: WATER; ALOE VERA LEAF; GLYCERIN; CARBOMER COPOLYMER TYPE A; .ALPHA.-TOCOPHEROL ACETATE, D-; AMINOMETHYLPROPANOL

Lieber's Hand Sanitizer: Advanced Regular

Active Ingredients

Ethyl Alcohol 65%

Purpose: Antiseptic

Purpose

Antiseptic

Uses

- helps reduce bacteria on the skin that could cause disease
- Recommended for repeated use

Directions

- Place enough product in your palm to thoroughly cover your hands
- Rub hands together briskly until dry
- Children under 6 years of age should be supervised when using this product.

Warnings

For external use only.

Flammable. Keep away from fire or flame.

Safety Instructions

Flammable, Keep away from fire and flame

Ask Doctor

Stop Use and Ask a doctor if irritation or redness develops

KEEP OUT OF REACH OF CHILDREN

If swallowed, get medical help or contact Poison Control right away

Other Information

Store below 110°F (43°C)
May discolor certain fabrics or surfaces.

Inactive Ingredients

water, glycerin, carbomer, aminomethyl propanol, fragrance, Aloe, Tocopheryl Acetate. Please review Label for further details